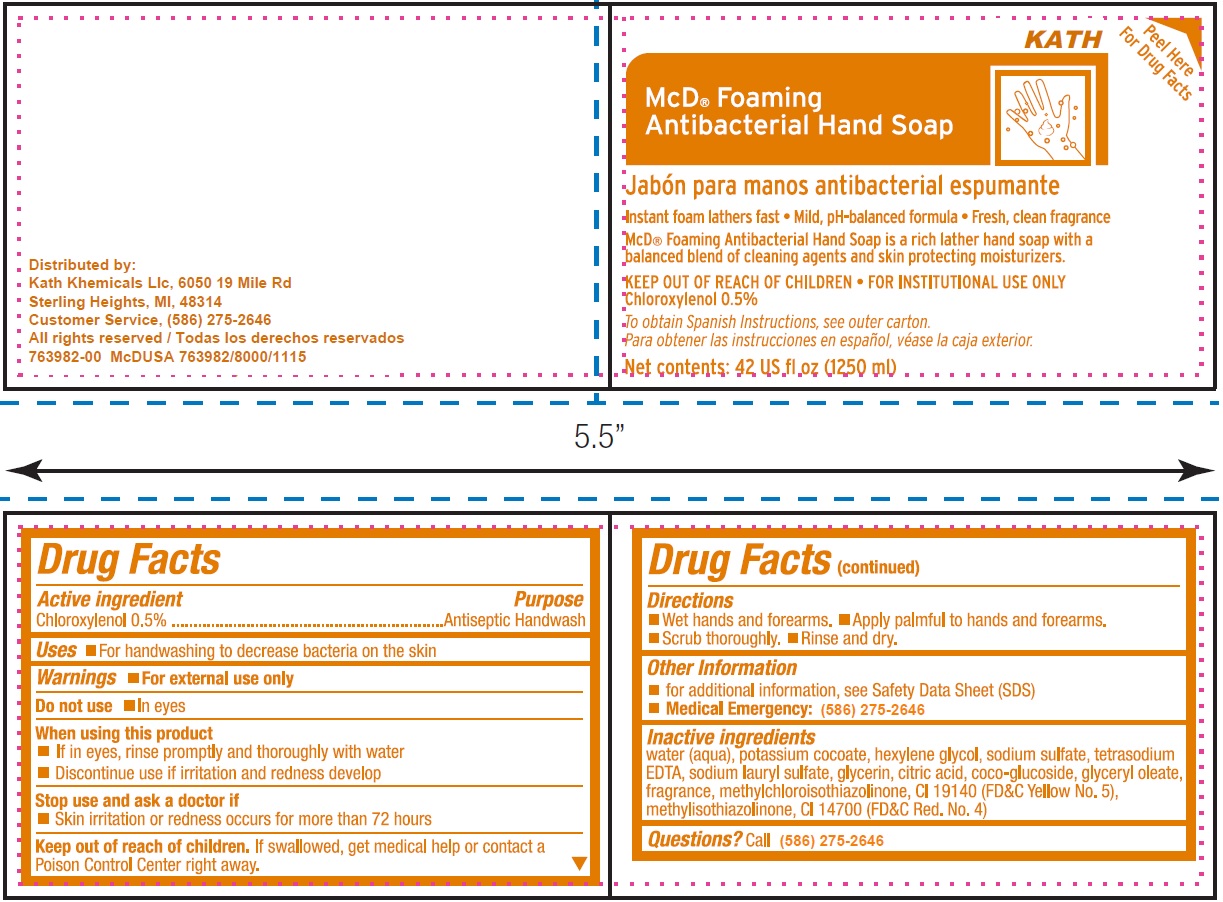 DRUG LABEL: McD Foaming Antibacterial Hand
NDC: 63301-001 | Form: LIQUID
Manufacturer: Kath Khemicals LLC
Category: otc | Type: HUMAN OTC DRUG LABEL
Date: 20250530

ACTIVE INGREDIENTS: CHLOROXYLENOL 5 mg/1 mL
INACTIVE INGREDIENTS: WATER; POTASSIUM COCOATE; HEXYLENE GLYCOL; SODIUM SULFATE; EDETATE SODIUM; SODIUM LAURYL SULFATE; GLYCERIN; CITRIC ACID MONOHYDRATE; COCO GLUCOSIDE; GLYCERYL OLEATE; METHYLCHLOROISOTHIAZOLINONE; FD&C YELLOW NO. 5; METHYLISOTHIAZOLINONE; FD&C RED NO. 4

McD Foaming Antibacterial Hand Soap

Active ingredient

Chloroxylenol 0.5%

Purpose

Antiseptic Handwash

Uses

- For handwashing to decrease bacteria on the skin

Warnings

- For external use only

Do not use

In eyes

When using this product

- If in eyes, rinse promptly and thoroughly with water
- Discontinue use if irritation and redness develop

Stop use and ask a doctor if

- Skin irritation or redness occurs for more than 72 hours

Keep out of reach of children.

If swallowed, get medical help or contact a Poison Control Center right away.

Directions

- Wet hands and forearms.
- Apply palmful to hands and forearms.
- Scrub thoroughly.
- Rinse and dry.

Other Information

- for additional information, see Safety Data Sheet (SDS)
- (586) 275-2646 Medical Emergency:

Inactive ingredients

water (aqua), potassium cocoate, hexylene glycol, sodium sulfate, tetrasodium EDTA, sodium lauryl sulfate, glycerin, citric acid, coco-glucoside, glyceryl oleate, fragrance, methylchloroisothiazolinone, CI 19140 (FD&C Yellow No. 5), methylisothiazolinone,, CI 14700 (FD&C Red. No. 4)

Questions?

Call (586) 275-2646